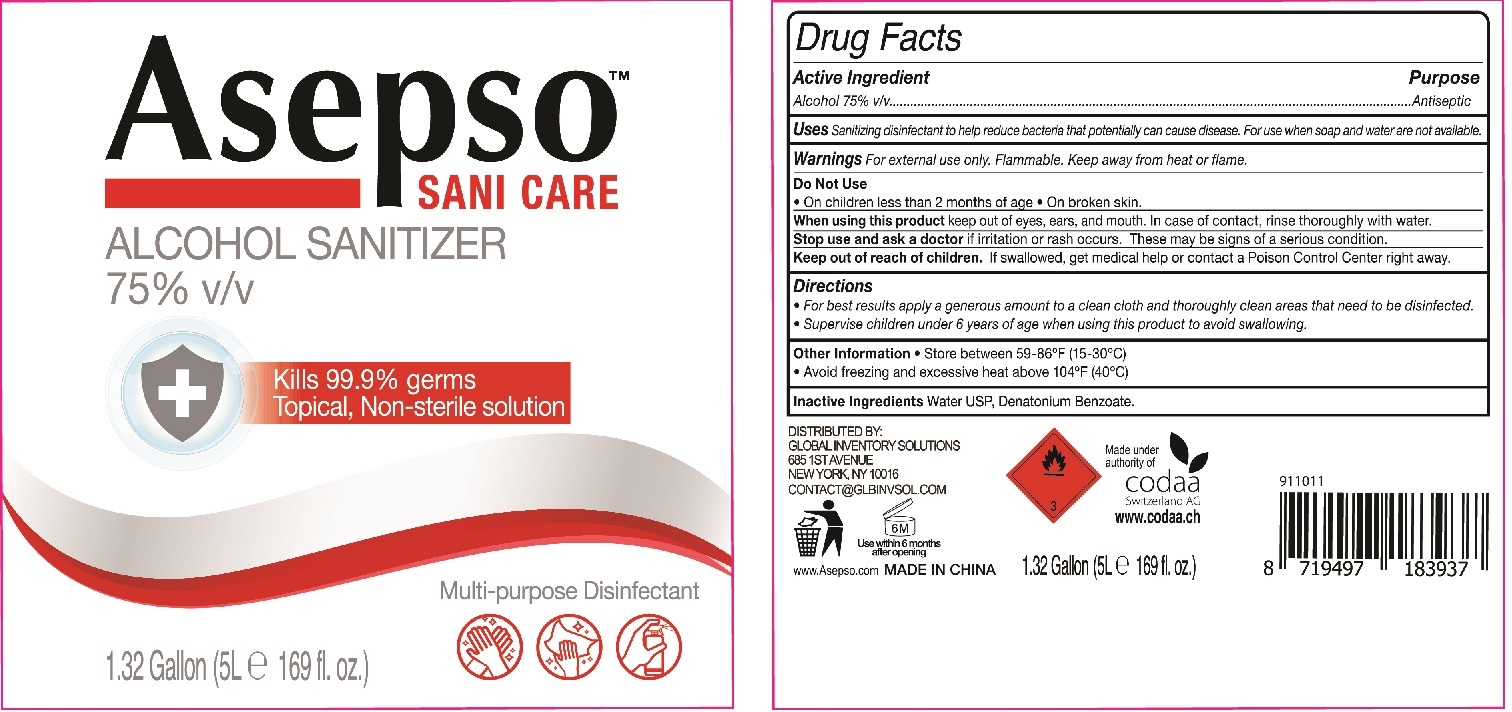 DRUG LABEL: Asepso Sani Care Alcohol Sanitizer
NDC: 73931-010 | Form: GEL
Manufacturer: Guangdong Essence Daily Chemical Co., Ltd
Category: otc | Type: HUMAN OTC DRUG LABEL
Date: 20200618

ACTIVE INGREDIENTS: ALCOHOL 75 mL/100 mL
INACTIVE INGREDIENTS: WATER; GLYCERIN; DENATONIUM BENZOATE

Active ingredient

Alcohol 75% v/v

Purpose

Antiseptic

Use

Sanitizing disinfectant to help reduce bacteria that potentially can cause disease. For use when soap ad water are not avilable.

Warnings

For external use only.

Flammable,

Keep away from heat and flame.

Do not use

- On children less than 2 months of age
- On broken skin.

When using this product keep out of eyes, ears, and mouth. In case of contact, rinse thoroughly with water.

Stop use and ask a doctor if irritation or rash occurs. These may be signs of a serious condition.

Keep out of reach of children.

If swallowed, get medical help or contact a Poison Control Center right away.

Directions

- For best results apply a generous amount to a clean cloth and thoroughly clean areas that need to be disinfectant.
- Supervise children under 6 years of age when using this product to avoid swallowing.

Inactive ingredients

Water USP, Denatonium Benzoate.

Other information

- Store between 59-86℉ (15-30℃)
- Avoid freezing and excessive heat above 104℉ (40℃)